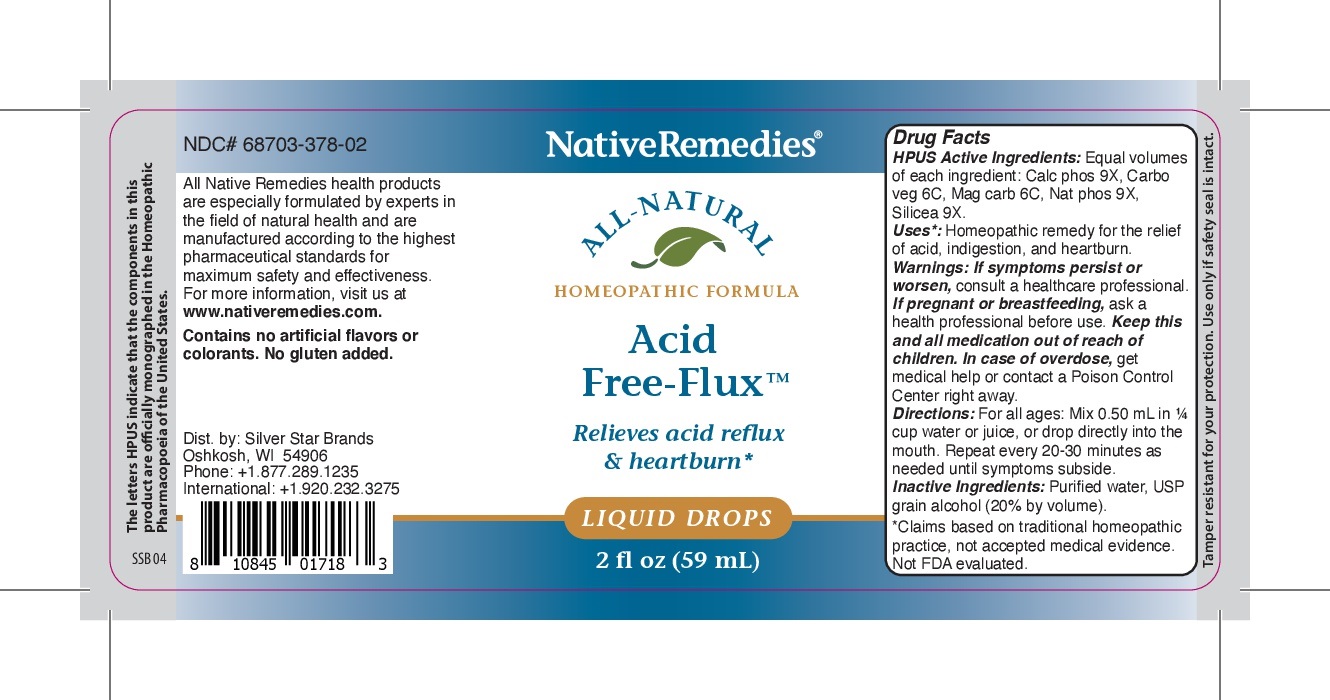 DRUG LABEL: NativeRemedies Acid Free-Flux
NDC: 68703-378 | Form: LIQUID
Manufacturer: Silver Star Brands
Category: homeopathic | Type: HUMAN OTC DRUG LABEL
Date: 20250101

ACTIVE INGREDIENTS: SODIUM PHOSPHATE, DIBASIC 9 [hp_X]/59 mL; ACTIVATED CHARCOAL 6 [hp_C]/59 mL; SILICON DIOXIDE 9 [hp_X]/59 mL; MAGNESIUM CARBONATE HYDROXIDE 6 [hp_C]/59 mL; CALCIUM PHOSPHATE 9 [hp_X]/59 mL
INACTIVE INGREDIENTS: WATER; ALCOHOL

NativeRemedies® Acid Free-Flux™

HPUS Active Ingredients: Equal volumes of each ingredient: Calc phos 9X, Carbo veg 6C, Mag carb 6C, Nat phos 9X, Silicea 9X.

Uses*:

Uses*: Homeopathic remedy for the relief of acid, indigestion, and heartburn.

*Claims baed on traditional homeopathic practice, not accepted medical evidence. Not FDA evaluated.

Warnings

Warnings: If symptoms persist or worsen, consulta healthcare professional. If pregnant or breastfeeding, ask a health professional before use. Keep this and all medication out of reach of children. In case of overdose, get medical help or contact a Poison Control Center right away.

Directions

Direcions: For all ages: Mix 0.50mL in 1/4 cup of water or juice, or drop directly into the mouth. Repeat every 20-30 minutes as needed until symptoms subside.

OTHER SAFETY INFORMATION

Contains no artificial flavors or colorants. No gluten added.

Tamper resistant for your protection. use only if safety seal is intact.

Inactive Ingredients

Inactive ingredients: Purified water, USP grain alcohol (20% by volume).

KEEP OUT OF REACH OF CHILDREN

Keep this and all medication out of erach of children.

PREGNANCY OR BREAST FEEDING

Relieves acid reflux & heartburn*

*Claims based on traditional homeopathic practice, not accepted medical evidence. Not FDA evaluated.

PURPOSE

Relieves acid reflux & heartburn*

*Claims based on traditional homeopathic practice, not accepted medical evidence. Not FDA evaluated.